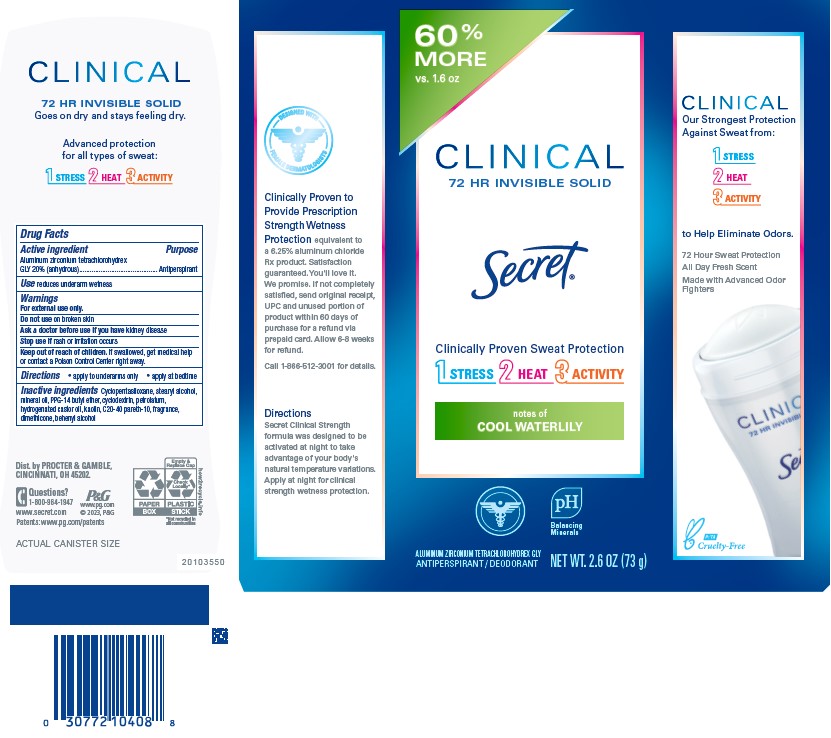 DRUG LABEL: Secret Clinical Invisible Cool Waterlily
NDC: 84126-069 | Form: STICK
Manufacturer: The Procter & Gamble Manufacturing Company
Category: otc | Type: HUMAN OTC DRUG LABEL
Date: 20251231

ACTIVE INGREDIENTS: ALUMINUM ZIRCONIUM TETRACHLOROHYDREX GLY 20 g/100 g
INACTIVE INGREDIENTS: CYCLODEXTRINS; CYCLOPENTASILOXANE; STEARYL ALCOHOL; MINERAL OIL; PPG-14 BUTYL ETHER; KAOLIN; PETROLATUM; HYDROGENATED CASTOR OIL; C20-40 PARETH-10; DIMETHICONE; BEHENYL ALCOHOL

Secret® Clinical Strength Invisible Cool Waterlily

Drug Facts

Active ingredient

Aluminum zirconium tetrachlorohydrex Gly 20% (anhydrous)

Purpose

Antiperspirant

Use

- reduces underarm wetness

Warnings

For external use only.

Do not use on broken skin

Ask a doctor before use if you have kidney disease

Stop use if rash or irritation occurs

Keep out of reach of children. If swallowed, get medical help or contact a Poison Control Center right away.

Directions

Apply to underarms only Apply at bedtime

Inactive ingredients

Cyclopentasiloxane, stearyl alcohol, mineral oil, PPG-14 butyl ether, cyclodextrin, petrolatum, hydrogenated castor oil, kaolin, C20-40 pareth-10, fragrance, dimethicone, behenyl alcohol

Questions?

1-800-964-1947

www.secret.com

Dist. by PROCTER & GAMBLE,
CINCINNATI, OH 45202.

PRINCIPAL DISPLAY PANEL - 73g Cylinder Carton

Secret®
CLINICAL
72 HR INVISIBLE SOLID

Clinically Proven Sweat Protection

notes of

COOL WATERLILY

ALUMINUM ZIRCONIUM TETRACHLOROHYDREX GLY
ANTIPERSPIRANT / DEODORANT

NET WT. 2.6 OZ (73 g)